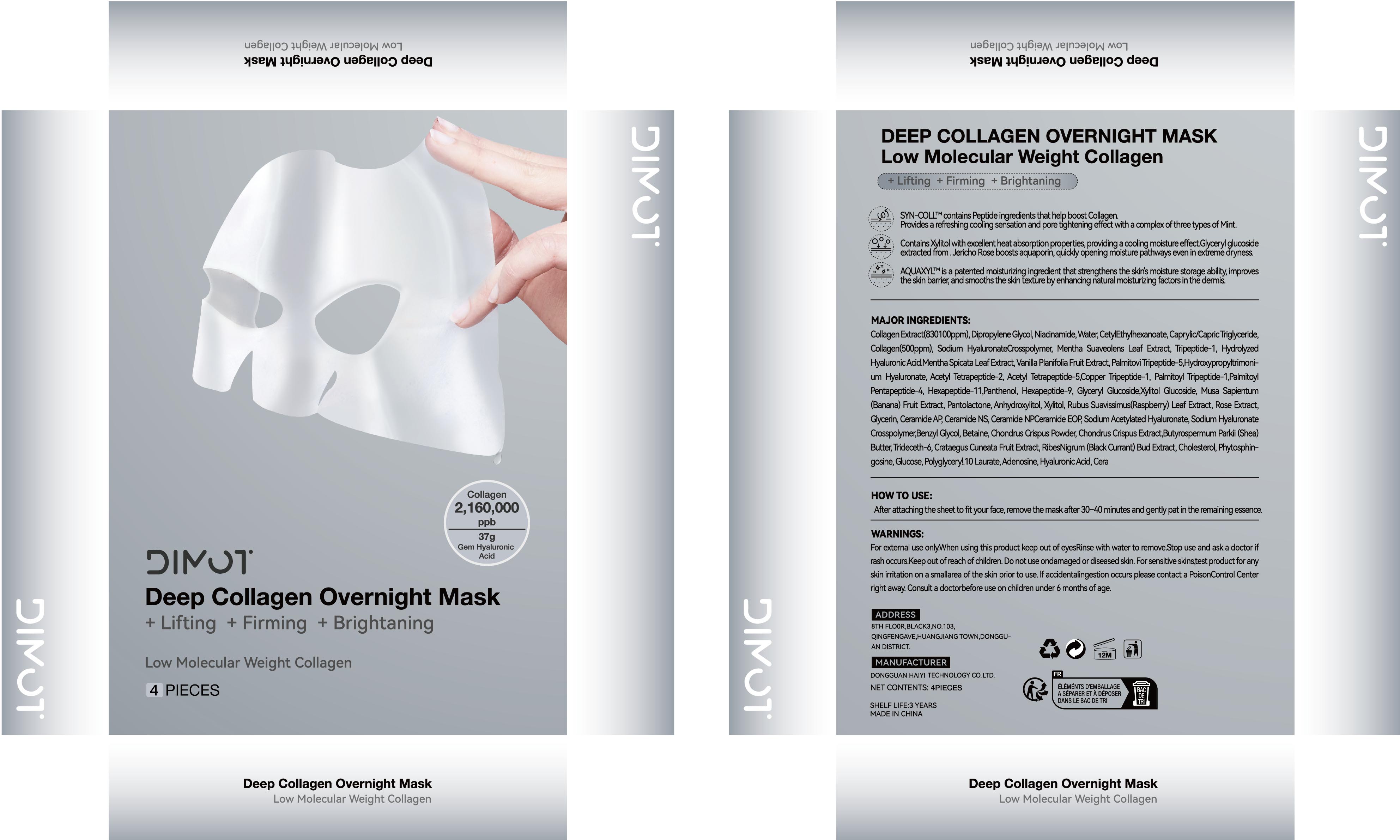 DRUG LABEL: Deep Collagen Anti Wrinkle Lifting Mask
NDC: 84732-067 | Form: PATCH
Manufacturer: Dongguan Haiyi Technology Co.,Ltd.
Category: otc | Type: HUMAN OTC DRUG LABEL
Date: 20241025

ACTIVE INGREDIENTS: HYALURONIC ACID 1 mg/100 g
INACTIVE INGREDIENTS: MENTHA SUAVEOLENS LEAF; NIACINAMIDE; DIPROPYLENE GLYCOL; WATER; TRIPEPTIDE-1; CETYL ETHYLHEXANOATE; CAPRYLIC/CAPRIC TRIGLYCERIDE; PEG-9 DIGLYCIDYL ETHER/SODIUM HYALURONATE CROSSPOLYMER; METHYL CARBOXYMETHYLPHENYL AMINOCARBOXYPROPYLPHOSPHONATE

Active ingredient

Hydrolyzed Hyaluronic Acid

Inactive ingredient

Collagen ·Dipropylene Glycol·Niacinamide·Aqua·Cetyl Ethylhexanoate·Caprylic/Capric Triglyceride·Sodium Hyaluronate Crosspolymer·Mentha Suaveolens Leaf Extract·Tripeptide-1

Purpose section

Smoothes and brightens the complexion for a glamorous glow.

Warning

For external use onlyWhen using this product keep out of eyesRinse with water to remove.Stop use and ask a doctorif
rash occurs.Keep outof reachof children.Do not use ondamaged or diseased skin.For sensitive skinstest product for any
skin iritation on a smallarea ofthe skin prior to use.lf accidentalingestion occurs please contact a PoisonControl Center
right away. Consult a doctorbefore use on children under6 months of age.

stop use

This product may cause allergic reactions in asmall number of people.
lf youexperience any discomfort,please stop using it immediately.

not use

Not suitable for use by children, pregnantor breast feeding people.

OUT OF CHILDREN

KEEP THE PRODUCT OUT OF REACH OF CHILDREN to

HOW TO USE

After attaching the sheetto fityourface,remove the mask after 30-40minutes and gentypatin the remaining essence

Dosage

Apply once or twice a week